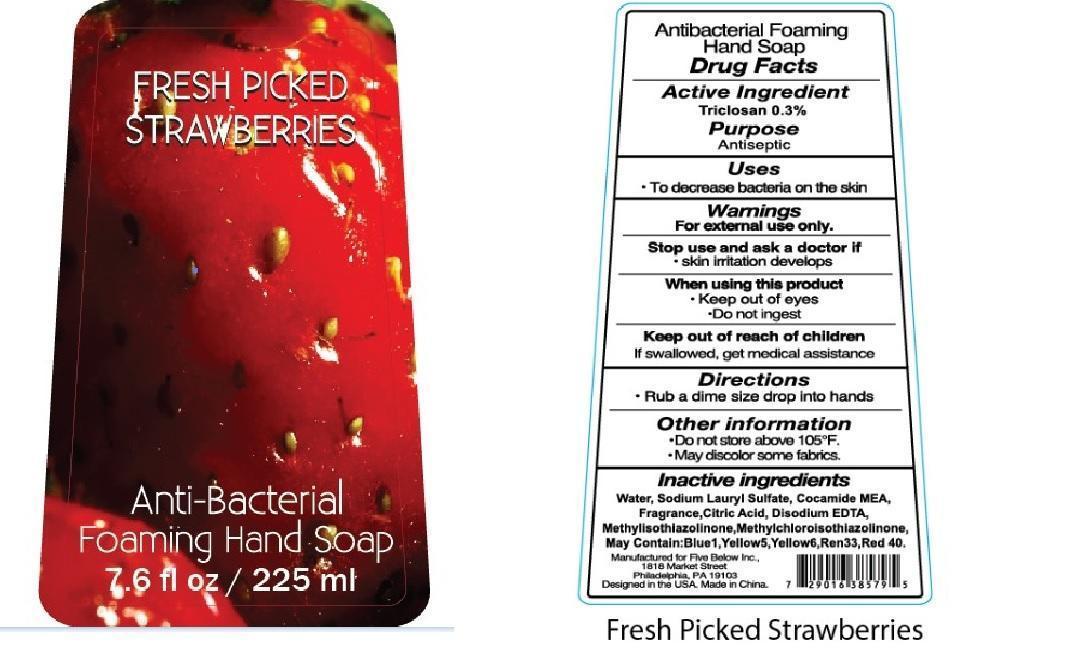 DRUG LABEL: Fresh Picked Strawberries Anti Bacterial Foaming Hand
NDC: 59021-006 | Form: LIQUID
Manufacturer: Five Below
Category: otc | Type: HUMAN OTC DRUG LABEL
Date: 20130413

ACTIVE INGREDIENTS: TRICLOSAN 0.3 g/100 mL
INACTIVE INGREDIENTS: WATER 82.009948 g/100 mL; SODIUM LAURETH SULFATE; COCO MONOETHANOLAMIDE; EDETATE DISODIUM; D&C RED NO. 33; FD&C BLUE NO. 1; FD&C YELLOW NO. 5; FD&C YELLOW NO. 6; FD&C RED NO. 40; ANHYDROUS CITRIC ACID; METHYLISOTHIAZOLINONE; METHYLCHLOROISOTHIAZOLINONE

Drug Fact

Active Ingredient

Triclsan 0.3%

Purpose

Antiseptic

Uses

To decrease bacteria on the skin

WARNINGS

For external use only

When using this product: Keep out of eyes. Do not ingest.

Stop use and ask a doctor if skin irritation develops

Keep out of reach of children. If swallowed, get medical assistance.

Directions

- Rub a dime size drop into hands

Other Information:

- Do not store above 105F
- May discolor some fabrics

Inactive Ingredient:

Deionized Water, Sodium Laurel Sulfate, Cocamide MEA, Fragrance, Citric Acid, Disodium EDTA, Methylisothiazolinone, Methylchloroisothiazolinone, may contain D and C Red No. 33, FD and C Red No. 40, FD and C Blue No. 1, FD and C Yellow No. 5, FD and C Yellow No. 6.

PACKAGE LABEL

lab